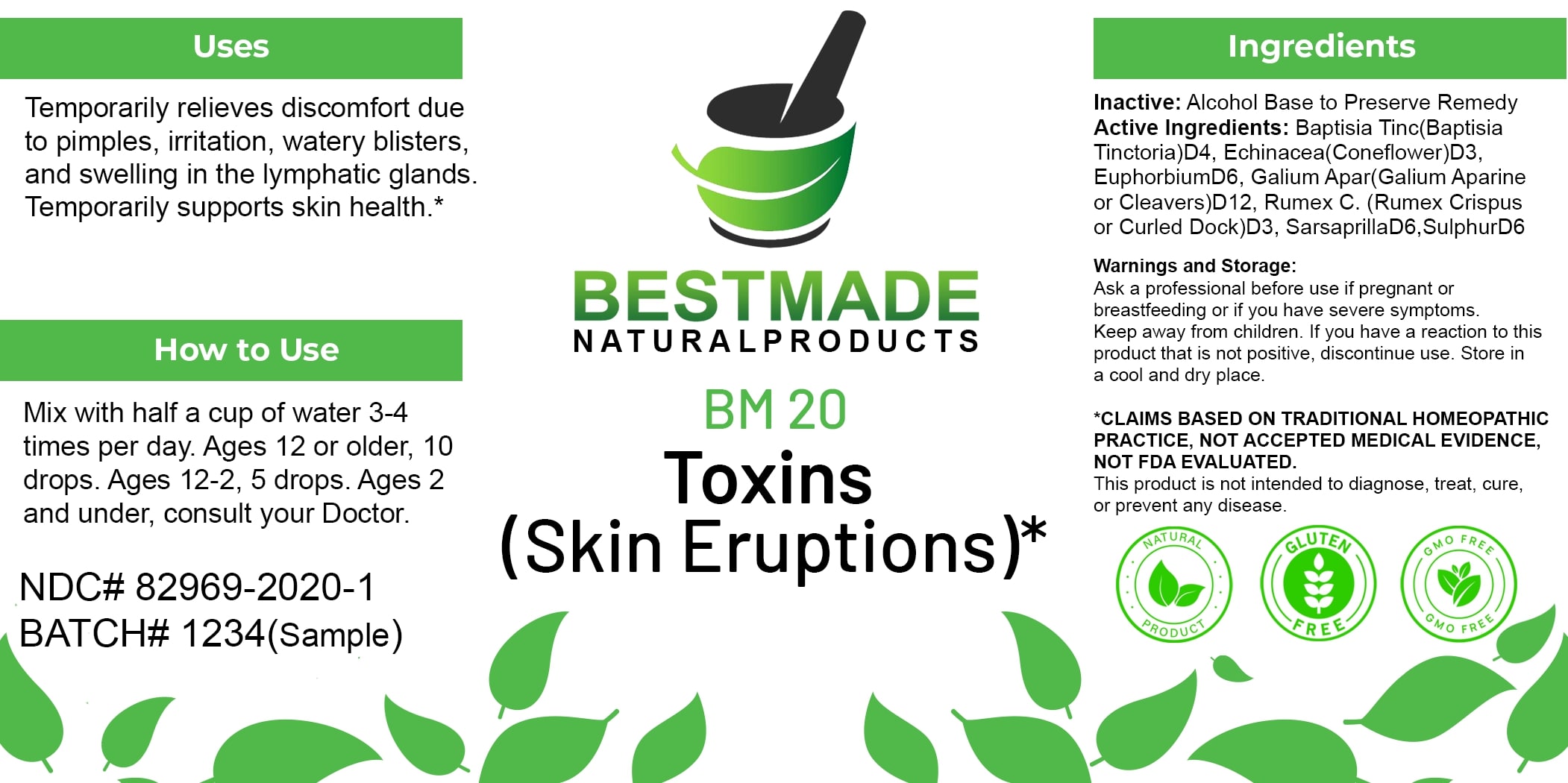 DRUG LABEL: Bestmade Natural Products BM20
NDC: 82969-2020 | Form: LIQUID
Manufacturer: Bestmade Natural Products
Category: homeopathic | Type: HUMAN OTC DRUG LABEL
Date: 20250122

ACTIVE INGREDIENTS: ECHINACEA ANGUSTIFOLIA 30 [hp_C]/30 [hp_C]; RUMEX CRISPUS ROOT 30 [hp_C]/30 [hp_C]; SMILAX ORNATA ROOT 30 [hp_C]/30 [hp_C]; SULFUR 30 [hp_C]/30 [hp_C]; GALIUM APARINE 30 [hp_C]/30 [hp_C]; BAPTISIA TINCTORIA ROOT 30 [hp_C]/30 [hp_C]; EUPHORBIA RESINIFERA RESIN 30 [hp_C]/30 [hp_C]
INACTIVE INGREDIENTS: ALCOHOL 30 [hp_C]/30 [hp_C]

BM20

DOSAGE AND ADMINISTRATION

How to Use
Mix with half a cup of water 3-4 times per day. Ages 12 or older, 10 drops. Ages 12-2, 5 drops. Ages 2 and under, consult your Doctor.

INACTIVE INGREDIENT

Ingredients
Inactive: Alcohol Base to Preserve Remedy

Uses
Temporarily relieves discomfort due to pimples, irritation, watery blisters, and swelling in the lymphatic glands. Temporarily supports skin health.*

*CLAIMS BASED ON TRADITIONAL HOMEOPATHIC PRACTICE, NOT ACCEPTED MEDICAL EVIDENCE, NOT FDA EVALUATED.
This product is not intended to diagnose, treat, cure, or prevent any disease.

Active Ingredients:

Baptisia Tinc (Baptisia Tinctoria) D4, Echinacea (Coneflower) D3, Euphorbium D6, Galium Apar (Galium Aparine or Cleavers) D12, Rumex C. (Rumex Crispus or Curled Dock) D3, Sarsaparilla D6, Sulphur D6

KEEP OUT OF REACH OF CHILDREN

Warnings and Storage:
Ask a professional before use if pregnant or breastfeeding or if you have severe symptoms. Keep away from children. If you have a reaction to this product that is not positive, discontinue use. Store in a cool and dry place.

Uses
Temporarily relieves discomfort due to pimples, irritation, watery blisters, and swelling in the lymphatic glands. Temporarily supports skin health.*

*CLAIMS BASED ON TRADITIONAL HOMEOPATHIC PRACTICE, NOT ACCEPTED MEDICAL EVIDENCE, NOT FDA EVALUATED.
This product is not intended to diagnose, treat, cure, or prevent any disease.

Warnings and Storage:
Ask a professional before use if pregnant or breastfeeding or if you have severe symptoms. Keep away from children. If you have a reaction to this product that is not positive, discontinue use. Store in a cool and dry place.

*CLAIMS BASED ON TRADITIONAL HOMEOPATHIC PRACTICE, NOT ACCEPTED MEDICAL EVIDENCE, NOT FDA EVALUATED.
This product is not intended to diagnose, treat, cure, or prevent any disease.

Entire package label